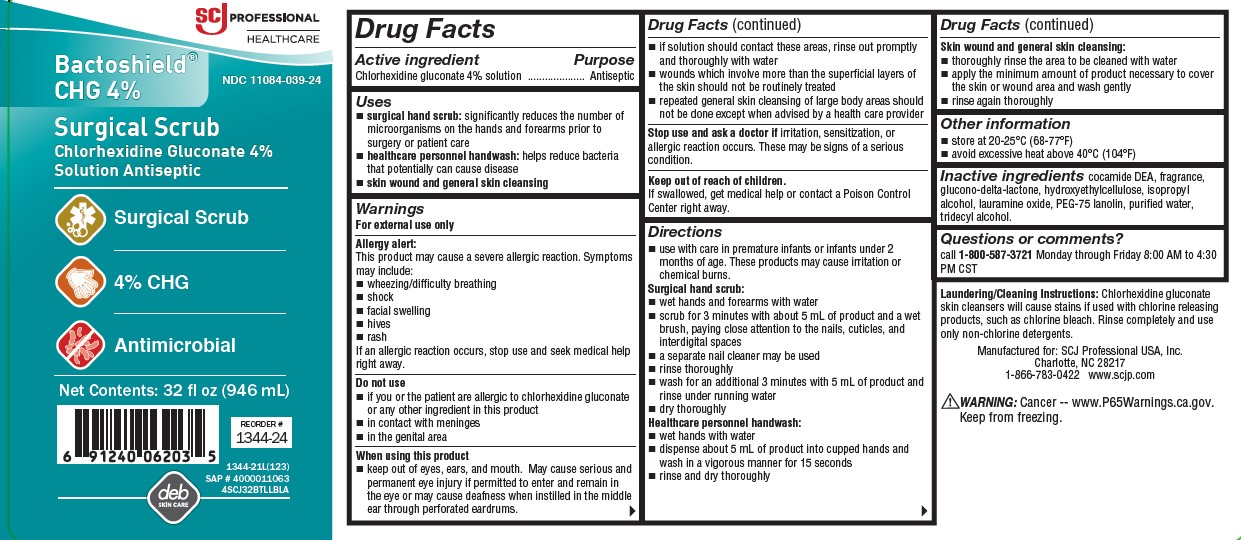 DRUG LABEL: Bactoshield CHG
NDC: 0116-0039 | Form: SOLUTION
Manufacturer: Xttrium Laboratories, Inc.
Category: otc | Type: HUMAN OTC DRUG LABEL
Date: 20251208

ACTIVE INGREDIENTS: CHLORHEXIDINE GLUCONATE 2 mg/100 mL
INACTIVE INGREDIENTS: LAURAMINE OXIDE; HYDROXYETHYL CELLULOSE (2000 CPS AT 1%); ISOPROPYL ALCOHOL; PEG-75 LANOLIN; TRIDECYL ALCOHOL; COCO DIETHANOLAMIDE; GLUCONOLACTONE; WATER

XTT COMP SCJ 32oz 4% CHG Bactoshield

Drug Facts

Active ingredient

Chlorhexidine gluconate 4% solution

Purpose

Antiseptic

Uses

- surgical hand scrub: significantly reduces the number of microorganisms on the hands and forearms prior to surgery or patient care
- healthcare personnel handwash: helps reduce bacteria that potentially can cause disease
- skin wound and general skin cleansing

Warnings

For external Use Only

Allergy Alert:

This product may cause a severe allergic reaction. Symptoms may include:

- wheezing/difficulty breathing
- shock
- facial swelling
- hives
- rash

If an allergic reaction occurs, stop use and seek medical help right away.

Do not use

- if you or the patient is allergic to chlorhexidine gluconate or any other ingredient in this product
- in contact with meninges
- in the genital area

When using this product

- keep out of eyes, ears, and mouth. May cause serious and permanent eye injury if permitted to enter and remain in the eye or may cause deafness when instilled in the middle ear through perforated eardrums.

- if solution should contact these areas, rinse out promptly and thoroughly with water
- wounds which involve more than the superficial layers of the skin should not be routinely treated
- repeated general skin cleansing of large body areas should not be done except when advised by a health care provider

Stop use and ask a doctor if

irritation, sensitization, or allergic reaction occurs. These may be signs of a serious condition.

Keep out of reach of children

If swallowed, get medical help or contact a Poison Control Center right away.

Directions

- use with care in premature infants or infants under 2 months of age. These products may cause irritation or chemical burns.

Surgical hand scrub:

- wet hands and forearms with water
- scrub for 3 minutes with about 5 mL of product and a wet brush, paying close attention to the nails, cuticles, and interdigital spaces
- a separate nail cleaner may be used
- rinse thoroughly
- wash for an additional 3 minutes with 5 mL of product and rinse under running water
- dry thoroughly

Healthcare personnel handwash:

- wet hands with water
- dispense about 5 mL of product into cupped hands and wash in a vigorous manner for 15 seconds
- rinse and dry thoroughly

Skin wound and general skin cleaning:

- thoroughly rinse the area to be cleaned with water
- apply the minimum amount of product necessary to cover the skin or wound area and wash gently
- rinse again thoroughly

Other information

- store at 20-25°C (68-77°F)
- avoid excessive heat above 40°C (104°F)

Inactive ingredients

cocamide DEA, fragrance, glucono-delta-lactone, hydroxyethylcellulose, isopropyl alcohol, lauramine oxide, PEG-75 lanolin, purified water, tridecyl alcohol

Questions or comments?

call 1-800-587-3721
Monday through Friday 8:00 AM to 4:30 PM CST

Laundering/Cleaning Instructions:

Chlorhexidine gluconate skin cleansers will cause stains if used with chlorine releasing products, such as chlorine bleach. Rinse completely and use only non-chlorine detergents.

Packaging

SCJ Professional

Healthcare

Bactoshield

CHG 4%

NDC 11084-039-24

Surgical Scrub

Chlorhexidine Gluconate 4% Solution Antiseptic

Surgical Scrub

4% CHG

Antimicrobial

Net Contents:32 fl oz (946 mL)

REORDER#

1344-24

SAP # 4000011063

1344-21L(123)

4SCJ32BTLLBLA

deb

SKIN CARE

Manufactured for: SCJ Professional USA, Inc.

Charlotte, NC 28217

1-866-783-0422 www.scjp.com

WARNING: Cancer -- www.P65Warnings.ca.gov. Keep from freezing.